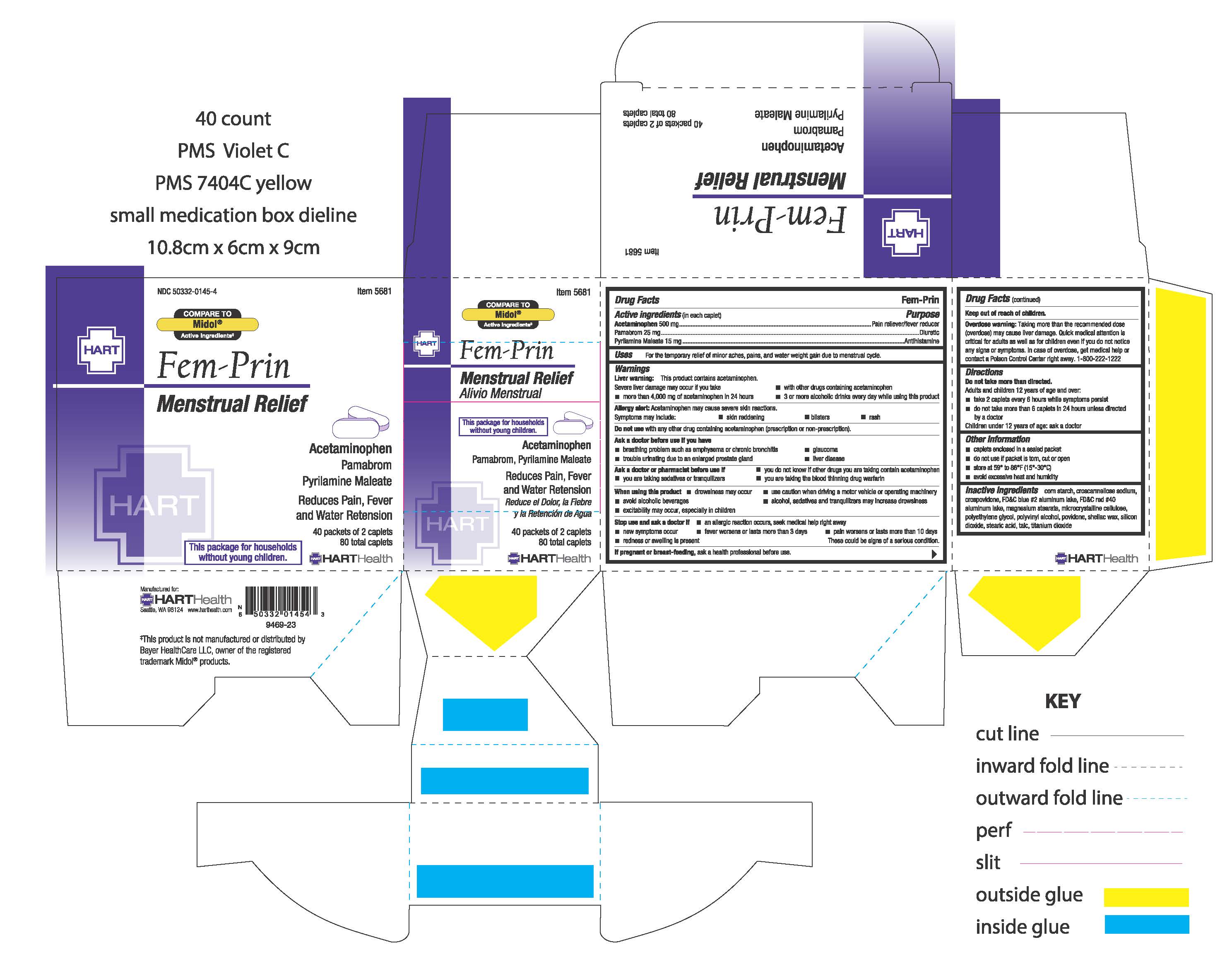 DRUG LABEL: FEM-PRIN
NDC: 50332-0145 | Form: TABLET, FILM COATED
Manufacturer: HART Health
Category: otc | Type: HUMAN OTC DRUG LABEL
Date: 20241204

ACTIVE INGREDIENTS: PAMABROM 25 mg/1 1; PYRILAMINE MALEATE 15 mg/1 1; ACETAMINOPHEN 500 mg/1 1
INACTIVE INGREDIENTS: POVIDONE, UNSPECIFIED; SILICON DIOXIDE; CROSCARMELLOSE SODIUM; FD&C BLUE NO. 2--ALUMINUM LAKE; POLYVINYL ALCOHOL, UNSPECIFIED; TITANIUM DIOXIDE; MAGNESIUM STEARATE; TALC; CROSPOVIDONE; STEARIC ACID; SHELLAC; STARCH, CORN; FD&C RED NO. 40; MICROCRYSTALLINE CELLULOSE; POLYETHYLENE GLYCOL, UNSPECIFIED

FEM-PRIN

Active ingredient (in each caplet)

Acetaminophen 500 mg

Pamabrom 25 mg

Pyrilamine maleate 15 mg

Purpose

Pain reliever/fever reducer

Diuretic

Antihistamine

Uses

for the temporary relief of minor aches, pain, and water weight gain due to mentrual cycle

Warnings

Liver warning: This product contains acetaminophen. Severe liver damage may occur if you take

■ more than 4,000 mg of acetaminophen in 24 hours

■ with other drugs containing acetaminophen

■ 3 or more alcoholic drinks every day while using this product

Allergy alert: Acetaminophen may cause severe skin reactions. Symptoms may include:

■ skin reddening

■ blisters

■ rash

Do not use

■ with any other drug containing acetaminophen (prescription or nonprescription).

Ask a doctor before use if you have

■ a breathing problem such as emphysema or chronic bronchitis

■ trouble urinating due to an enlarged prostate gland

■ liver disease

■ glaucoma

Ask a doctor or pharmacist before use if

■ you do not know if other drugs you are taking contain acetaminophen

■ you are taking sedatives or tranquilizers

■ you are taking the blood thinning drug warfarin

When using this product

■ drowsiness may occur

■ avoid alcoholic beverages

■ alcohol, sedatives and tranquilizers may increase drowsiness

■ use caution when driving a motor vehicle or operating machinery

■ excitability may occur, especially in children

Stop use and ask a doctor if

■ an allergic reaction occurs, seek medical help right away

■ fever worsens or lasts more than 3 days

■ pain worsens or lasts more than 10 days

■ new symptoms occur

■ redness or swelling is present

These could be signs of a serious condition.

PREGNANCY OR BREAST FEEDING

If pregnant or breast-feeding, ask a health professional before use.

Keep out of reach of children.

Directions

Do not take more than directed

Adults and children 12 years of age and over

■ take 2 caplets every 6 hours while symptoms persist

■ do not take more than 6 caplets in 24 hours unless directed by a doctor

Children under 12 years: ask a doctor

Other information:

■ caplets enclosed in a sealed packet

■ do not use if packet is torn, cut or open

■ store at 59° to 86°F (15°-30°C)

■ avoid excessive heat and humidity

Inactive ingredients

corn starch, croscarmellose sodium, crospovidone, FD&C blue #2 aluminum lake, FD&C red #40 aluminum lake, magnesium stearate, microcrystalline cellulose, polyethylene glycol, polyvinyl alcohol, povidone, shellac wax, silicon dioxide, stearic acid, talc, titanium dioxide